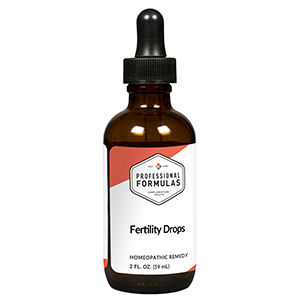 DRUG LABEL: Fertility Drops
NDC: 63083-2174 | Form: LIQUID
Manufacturer: Professional Complementary Health Formulas
Category: homeopathic | Type: HUMAN OTC DRUG LABEL
Date: 20190815

ACTIVE INGREDIENTS: LACHESIS MUTA VENOM 8 [hp_X]/59 mL; MERCURY 12 [hp_X]/59 mL; CHASTE TREE FRUIT 6 [hp_X]/59 mL; GOLD 6 [hp_X]/59 mL; SODIUM BORATE 6 [hp_X]/59 mL; OYSTER SHELL CALCIUM CARBONATE, CRUDE 6 [hp_X]/59 mL; CYCLAMEN PURPURASCENS TUBER 6 [hp_X]/59 mL; CYPRIPEDIUM PARVIFLORUM VAR. PUBESCENS ROOT 6 [hp_X]/59 mL; DIOSCOREA VILLOSA TUBER 6 [hp_X]/59 mL; IRON 6 [hp_X]/59 mL; HYOSCYAMUS NIGER 6 [hp_X]/59 mL; STRYCHNOS IGNATII SEED 6 [hp_X]/59 mL; IODINE 6 [hp_X]/59 mL; POTASSIUM DICHROMATE 6 [hp_X]/59 mL; WOOD CREOSOTE 6 [hp_X]/59 mL; SODIUM CARBONATE 6 [hp_X]/59 mL; SODIUM CHLORIDE 6 [hp_X]/59 mL; NITRIC ACID 6 [hp_X]/59 mL; NUTMEG 6 [hp_X]/59 mL; BOS TAURUS OVARY 6 [hp_X]/59 mL; BOS TAURUS PITUITARY GLAND, POSTERIOR 6 [hp_X]/59 mL; PULSATILLA MONTANA WHOLE 6 [hp_X]/59 mL; SEPIA OFFICINALIS JUICE 6 [hp_X]/59 mL; CAPSELLA BURSA-PASTORIS WHOLE 6 [hp_X]/59 mL; SUS SCROFA UTERUS 6 [hp_X]/59 mL; VIBURNUM OPULUS BARK 6 [hp_X]/59 mL
INACTIVE INGREDIENTS: ALCOHOL; WATER

C174

ACTIVE INGREDIENTS

Lachesis mutus 8X, 12X
Mercurius vivus 12X
and all the following at 6X, 12X:
Agnus castus
Aurum metallicum
Borax
Calcarea carbonica
Cyclamen europaeum
Cypripedium pubescens
Dioscorea villosa
Ferrum metallicum
Hyoscyamus niger
Ignatia amara
Iodium
Kali bichromicum
Kreosotum
Natrum carbonicum
Natrum muriaticum
Nitricum acidum
Nux moschata
Ovary
Pituitary
Pulsatilla
Sepia
Thlaspi bursa-pastoris
Uterus
Viburnum opulus

QUESTIONS

Professional Formulas

PO Box 2034 Lake Oswego, OR 97035

INDICATIONS

For the temporary relief of infertility symptoms including irregular, painful, or heavy menses, changes in sexual desire, or weight gain.*

PURPOSE

*Claims based on traditional homeopathic practice, not accepted medical evidence. Not FDA evaluated.

WARNINGS

In case of overdose, get medical help or contact a poison control center right away.

Keep out of the reach of children.

PREGNANCY OR BREAST FEEDING

If pregnant or breastfeeding, ask a healthcare professional before use.

DIRECTIONS

Place drops under tongue 30 minutes before/after meals. Adults and children 12 years and over: Take 10 drops up to 3 times per day. Consult a physician for use in children under 12 years of age. Not intended for use in infants.

OTHER INFORMATION

Tamper resistant. If seal is broken, do not use. After opening, close container tightly and store at room temperature away from heat.

INACTIVE INGREDIENTS

20% ethanol, purified water.

LABEL

Est 1985

Professional Formulas

Complementary Health

Fertility Drops

Homeopathic Remedy

2 FL. OZ. (59 mL)